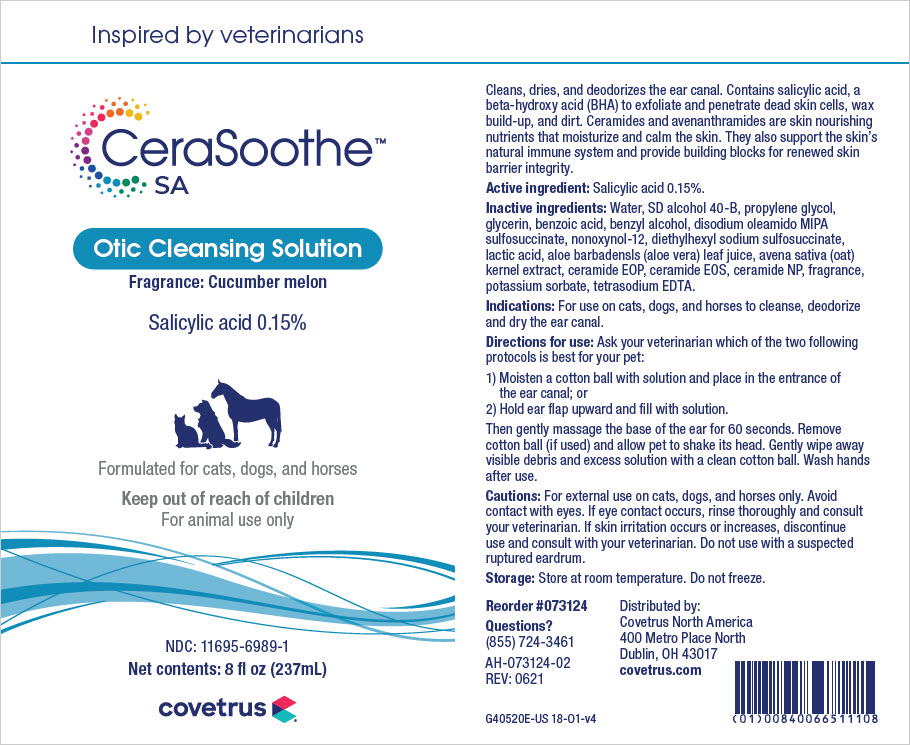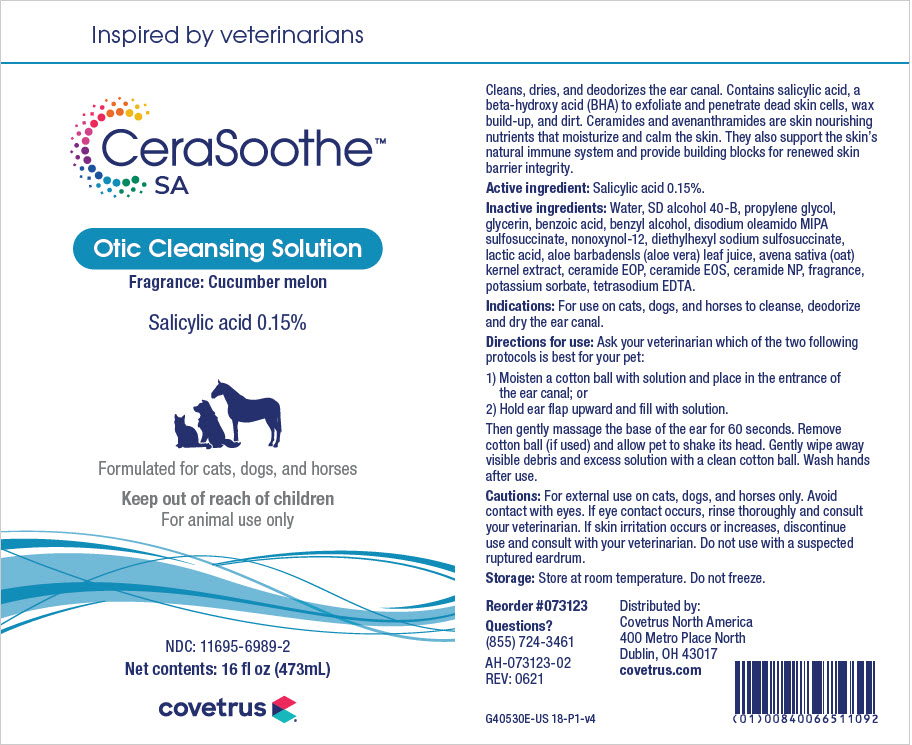 DRUG LABEL: CeraSoothe
NDC: 11695-6989 | Form: SOLUTION
Manufacturer: Butler Animal Health Supply, LLC dba Covetrus North America
Category: animal | Type: OTC ANIMAL DRUG LABEL
Date: 20250910

ACTIVE INGREDIENTS: SALICYLIC ACID 1.5 mg/1 mL
INACTIVE INGREDIENTS: WATER; ALCOHOL; PROPYLENE GLYCOL; GLYCERIN; BENZOIC ACID; BENZYL ALCOHOL; DISODIUM OLEAMIDO MIPA-SULFOSUCCINATE; NONOXYNOL-12; DOCUSATE SODIUM; LACTIC ACID, UNSPECIFIED FORM; ALOE VERA LEAF; AVENANTHRAMIDES; CERAMIDE 1; CERAMIDE EOS; CERAMIDE NP; POTASSIUM SORBATE; EDETATE SODIUM

DESCRIPTION

CeraSoothe SA

Otic Cleansing Solution

Fragrance: Cucumber melon

Formulated for cats, dogs, and horses

Cleans dries and deodorizes the ear canal. Contains salicylic acid, a beta-hydroxy acid (BHA) to exfoliate and penetrate dead skin cells, wax build-up and dirt. Ceramides and avenanthramides are skin nourishing nutrients that moisturize and calm the skin. They also support the skin's natural immune system and provide building blocks for renewed skin barrier integrity.

Active ingredients: Salicylic acid 0.15%.

Inactive ingredients: Water, SD alcohol 40-B, propylene glycol, glycerin, benzoic acid, benzyl alcohol, disodium oleamido MIPA sulfosuccinate, nonoxynol-12, diethylhexyl sodium sulfosuccinate, lactic acid, aloe barbadensis (aloe vera) leaf juice, avena sative (oat) kernel oil, ceramide EOP, ceramide EOS, ceramide NP, fragrance, potassium sorbate, tetrasodium EDTA.

INDICATIONS AND USAGE

Indications: For use on cats, dogs, and horses to cleanse, deodorize and dry the ear canal.

Directions for use: Ask your veterinarian which of the two following protocols is best for your pet:

1) Moisten a cotton ball with solution and place at the entrance of the ear canal; or

2) Hold ear flap upward and fill with solution.

Then gently massage the base of the ear for 60 seconds. Remove cotton ball (if used) and allow pet to shake its head. Gently wipe away visible debris and excess solution with a clean cotton ball. Wask hands after use.

WARNINGS AND PRECAUTIONS

Cautions: For external use on cats, dogs, and horses only. Avoid contact with the eyes. If eye contact occurs, rinse thoroughly and consult your veterinarian. If skin irritation occurs or increases, discontinue use and consult with your veterinarian. Do not use with a suspected ruptured eardrum.

Storage: Store at room temperature. Do not freeze.

Questions?

(855) 724-3461

Distributed by:

Covetrus North America

400 Metro Place North

Dublin, OH 43017

covetrus.com

PRINCIPAL DISPLAY PANEL - 237 mL Bottle Label

Inspired by veterinarians

CeraSoothe™
SA

Otic Cleansing Solution
Fragrance: Cucumber melon

Salicylic acid 0.15%

Formulated for cats, dogs, and horses

Keep out of reach of children
For animal use only

NDC: 11695-6989-1
Net contents: 8 fl oz (237mL)

covetrus

PRINCIPAL DISPLAY PANEL - 473 mL Bottle Label

Inspired by veterinarians

CeraSoothe™
SA

Otic Cleansing Solution
Fragrance: Cucumber melon

Salicylic acid 0.15%

Formulated for cats, dogs, and horses

Keep out of reach of children
For animal use only

NDC: 11695-6989-2
Net contents: 16 fl oz (473mL)

covetrus